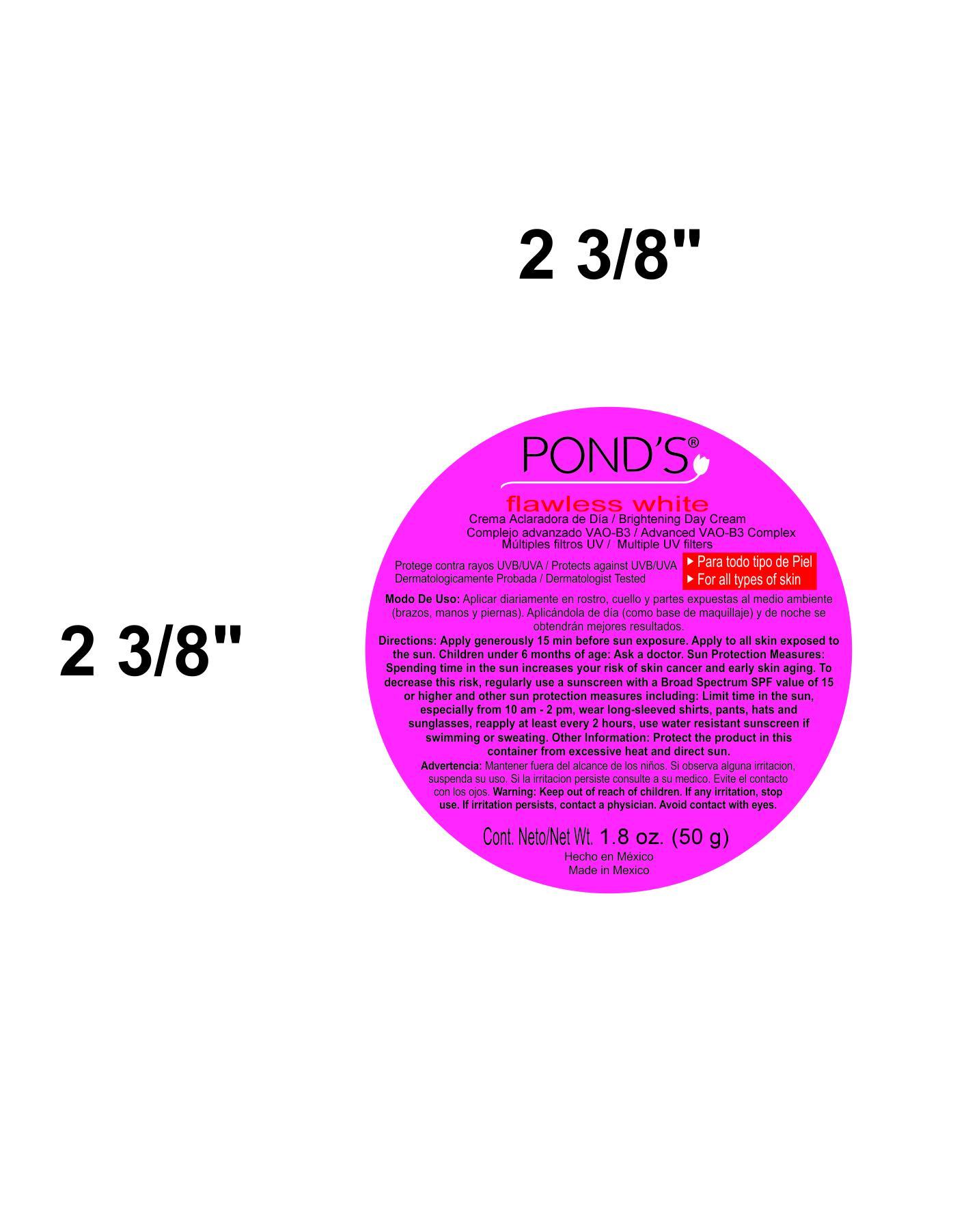 DRUG LABEL: PONDS
NDC: 51769-890 | Form: CREAM
Manufacturer: ALL NATURAL DYNAMICS
Category: otc | Type: HUMAN OTC DRUG LABEL
Date: 20130902

ACTIVE INGREDIENTS: AVOBENZONE 3 g/100 g
INACTIVE INGREDIENTS: Stearic Acid; Niacinamide; Isopropyl Myristate; GLYCERYL MONOSTEARATE; EDETATE DISODIUM; OCTINOXATE; GLYCERIN; TROLAMINE; CETYL ALCOHOL; Dimethicone; METHYLPARABEN; GLUTAMIC ACID; SODIUM PYRROLIDONE CARBOXYLATE; TITANIUM DIOXIDE; PROPYLPARABEN; ALLANTOIN; .ALPHA.-TOCOPHEROL ACETATE; SODIUM HYDROXIDE; SODIUM ASCORBYL PHOSPHATE; ALUMINUM HYDROXIDE; ISOMETHYL-.ALPHA.-IONONE; BENZYL SALICYLATE; BUTYLPHENYL METHYLPROPIONAL; .BETA.-CITRONELLOL, (R)-; .ALPHA.-HEXYLCINNAMALDEHYDE; HYDROXYISOHEXYL 3-CYCLOHEXENE CARBOXALDEHYDE; WATER

Ponds VAO-B3

Warnings:

For external use only. Avoid contact with eyes. If product gets into eyes, rinse thoroughly with water.

Directions:

Apply daily to ace and neck. For best results, apply during the morning (as a base for your make-up) and at night.

Discontinue use and consult a physician:

If you experience some irritation, rash or other adverse reaction.

Keep out of reach of children.

Ingredients:

Water, Stearic Acid, Niacinamide, Isopropyl Myristate,GLYCERYL MONOSTEARATE, EDETATE DISODIUM, OCTINOXATE, GLYCERIN, CETYL ALCOHOL, Dimethicone, METHYLPARABEN, GLUTAMIC ACID, SODIUM PYRROLIDONE CARBOXYLATE, TITANIUM DIOXIDE, PROPYLPARABEN, ALLANTOIN, .ALPHA.-TOCOPHEROL ACETATE, SODIUM HYDROXIDE, SODIUM ASCORBYL PHOSPHATE, ALUMINUM HYDROXIDE, ISOMETHYL-.ALPHA.-IONONE, BENZYL SALICYLATE, BUTYLPHENYL METHYLPROPIONAL, .BETA.-CITRONELLOL, (R)-, .ALPHA.-HEXYLCINNAMALDEHYDE, HYDROXYISOHEXYL 3-CYCLOHEXENE CARBOXALDEHYDE